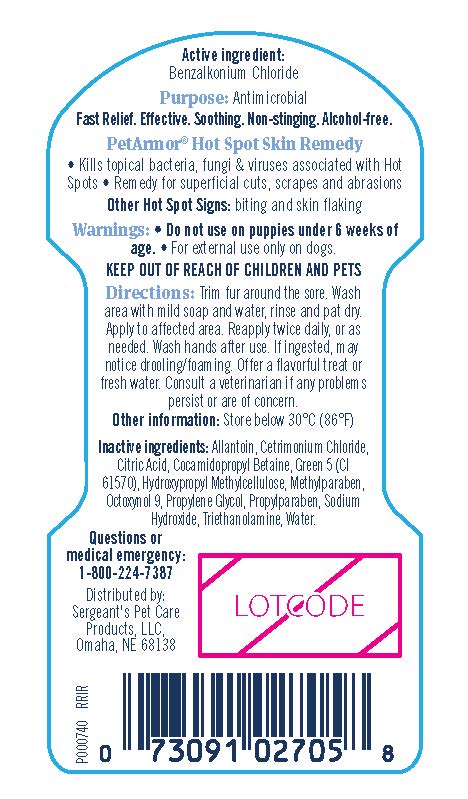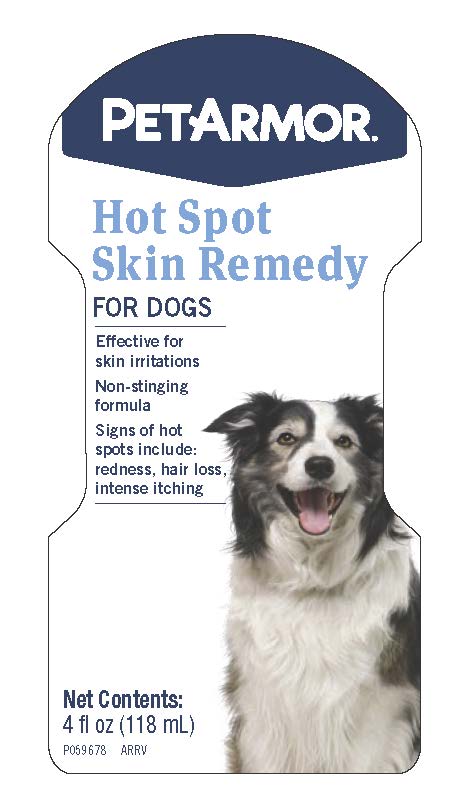 DRUG LABEL: Benzalkonium Chloride
NDC: 21091-002 | Form: GEL
Manufacturer: Sergeants Pet Care Products LLC
Category: animal | Type: OTC ANIMAL DRUG LABEL
Date: 20241205

ACTIVE INGREDIENTS: Benzalkonium Chloride 0.13 g/118 mL
INACTIVE INGREDIENTS: ALLANTOIN; CETRIMONIUM CHLORIDE; CITRIC ACID MONOHYDRATE; COCAMIDOPROPYL BETAINE; D&C GREEN NO. 5; HYPROMELLOSES; METHYLPARABEN; OCTOXYNOL-9; PROPYLENE GLYCOL; PROPYLPARABEN; SODIUM HYDROXIDE; TROLAMINE; WATER

PETARMOR Hot Spot Skin Remedy

Active Ingredient:

Benzalkonium Chloride

Purpose: Antimicrobial

Fast Relief. Effective. Soothing. Non-stinging. Alcohol-free.

PetArmor Hot Spot Skin Remedy

- Kills topical bacteria, fungi & viruses associated with Hot Spots
- Remedy for superficial cuts, scrapes and abrasions

Other Hot Spot Signs: biting and skin flaking

Warnings:

Do not use on puppies under 6 weeks of age. For external use only on dogs.

KEEP OUT OF REACH OF CHILDREN AND PETS

Directions:

Trim fur around the sore. Wash the area with mild soap and water, rinse and pat dry. Apply to affected area. Reapply twice daily, or as needed. Wash hands after use. If ingested, may notice drooling/foaming. Offer a flavorful treat or fresh water. Consult a veterinarian if any problems persist or are of concern.

Other information:

Store Below 30°C (86°F)

Inactive Ingredients:

Allantoin, Cetrimonium Chloride, Citric Acid, Cocamidopropyl Betaine, Green 5 (Cl 61570), Hydroxypropyl Methylcellulose, Methylparaben, Octoxynol 9, Propylene Glycol, Propylparaben, Sodium Hydroxide, Triethanolamine, Water.